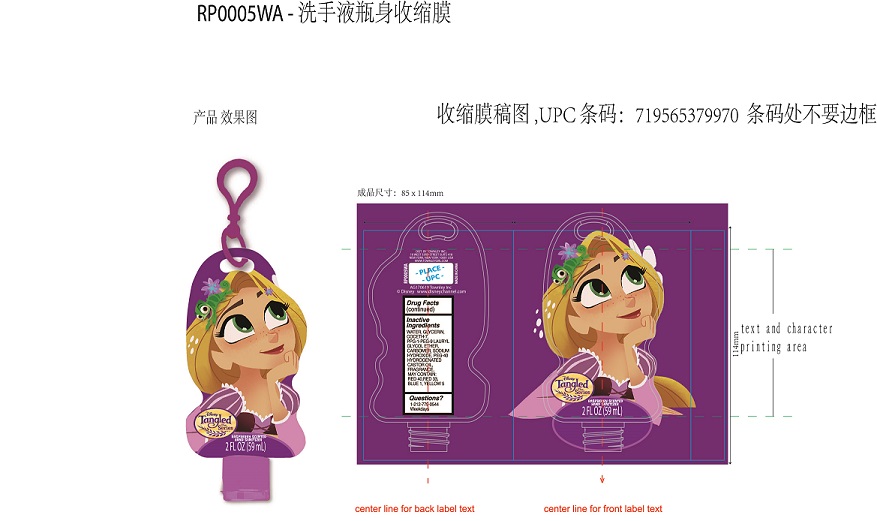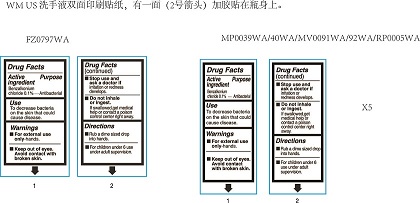 DRUG LABEL: Raspberry Scented Hand Sanitizer
NDC: 69795-025 | Form: GEL
Manufacturer: Foshan Jinxiong Technology Co., Ltd
Category: otc | Type: HUMAN OTC DRUG LABEL
Date: 20170609

ACTIVE INGREDIENTS: BENZALKONIUM CHLORIDE 0.1 g/100 g
INACTIVE INGREDIENTS: SODIUM HYDROXIDE; FD&C RED NO. 40; D&C RED NO. 33; FD&C BLUE NO. 1; FD&C YELLOW NO. 5; WATER; GLYCERIN; COCETH-7; PPG-1-PEG-9 LAURYL GLYCOL ETHER; CARBOMER COPOLYMER TYPE A; POLYOXYL 40 HYDROGENATED CASTOR OIL

Active Ingredient

Benzalkonium Chloride 0.1%

Purpose

Antibacterial

Keep out of reach of children.

Warnings

- For external use only - hands.
- Keep out of eyes. Avoid contact with broken skin.
- Stop use and ask a doctor if irritation or redness develops.
- Do not inhale or ingest. If swallowed, get medical help or contact a poison control center right away,

Directions

- Rub a dime sized drop into hands.
- For children under 6 use under adult supervision.

Inactive Ingredients

water, glycerin, coceth-7, PPG-1-PEG-9 lauryl glycol ether, carbomer, sodium hydroxide, PEG-40 hydrogenated castor oil, fragrance, Red 40, Red 33, Blue 1, Yellow 6

Use

To decrease bacteria on the skin that could cause disease.